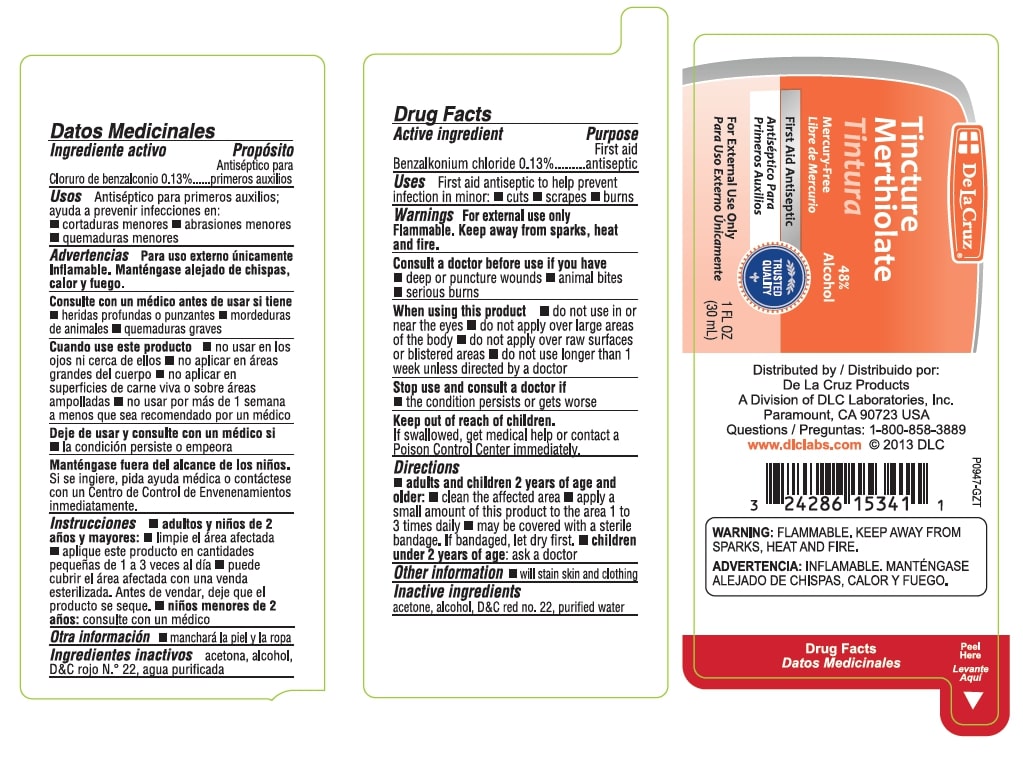 DRUG LABEL: Tincture Merthiolate
NDC: 24286-1532 | Form: TINCTURE
Manufacturer: DLC Laboratories, Inc
Category: otc | Type: HUMAN OTC DRUG LABEL
Date: 20231218

ACTIVE INGREDIENTS: BENZALKONIUM CHLORIDE 1.3 mg/1 mL
INACTIVE INGREDIENTS: ACETONE; ALCOHOL; D&C RED NO. 22; WATER

De La Cruz Tincture Merthiolate

Active Ingredient

Benzalkonium chloride 0.13%

Purpose

First Aid Antiseptic

Uses

First aid antiseptic to help prevent infection in minor:
cuts - scrapes - burns

Warnings

For external use only.

Flammable. Keep away from sparks, heat and fire.
Consult a doctor before use if you have - deep or puncture wounds - animal bites - serious burns

When using this product

- do not use in or near the eyes
- do not apply in large quantities or over large areas of the body
- do not apply over raw surtaces or blistered areas
- do not use longer than 1 week unless directed by a doctor

Stop use and consult a doctor if

- the condition persists or gets worse

Keep out of reach of children.

II swallowed, get medical help or contact a Poison Control Center immediately.

Directions

- adults and children 2 years of age and older: clean the affected area
- apply a small amount of this product to the area 1 to 3 times daily _ may be covered with a sterile bandage. If bandaged, let dry first
- children under 2 years of age: ask a doctor

Other Information

- will stain skin and clothing

Inactive Ingredients

acetone, alcohol, DandC red no. 22, purified water

Product Labeling

Tincture Merthiolate

48% Alcohol

Mercury Free

First Aid Antiseptic

For External Use Only

1 FL OZ (30 mL)

Distributed by
De La Cruz Products
A Division of DLC Laboratories, Inc.
Paramount, CA 90723 USA
Questions: 1-800-858-3889
www.dlclabs.com

Warnings: FLAMMABLE, KEEP AWAY FROM SPARKS, HEAT AND FIRE.